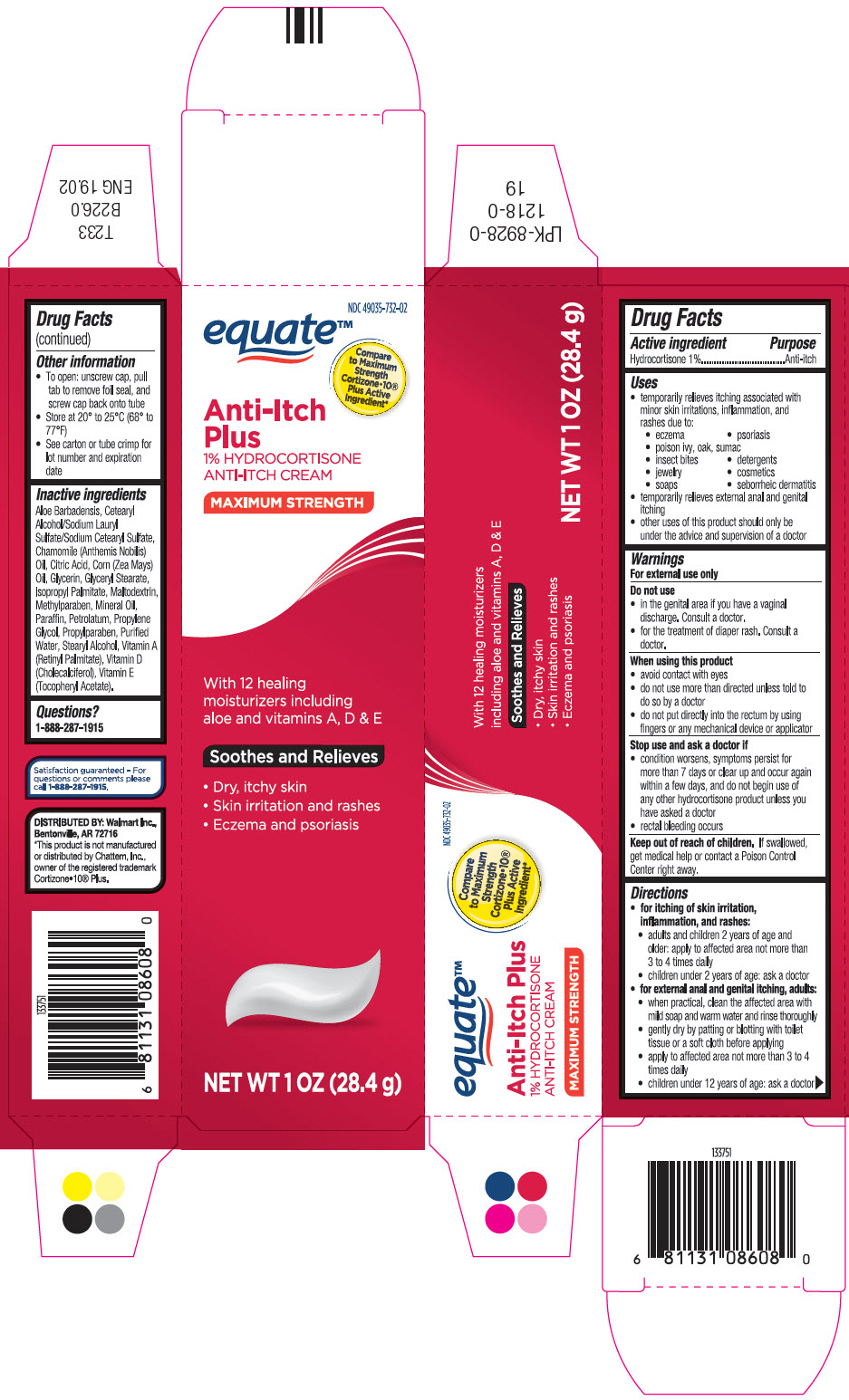 DRUG LABEL: Hydrocortisone anti-itch plus
NDC: 49035-732 | Form: CREAM
Manufacturer: Wal-Mart Stores, Inc.
Category: otc | Type: HUMAN OTC DRUG LABEL
Date: 20250716

ACTIVE INGREDIENTS: HYDROCORTISONE 10 mg/1 g
INACTIVE INGREDIENTS: CHAMOMILE FLOWER OIL; CITRIC ACID MONOHYDRATE; CORN OIL; GLYCERIN; ISOPROPYL PALMITATE; MALTODEXTRIN; METHYLPARABEN; MINERAL OIL; PARAFFIN; PETROLATUM; PROPYLENE GLYCOL; PROPYLPARABEN; WATER; STEARYL ALCOHOL; VITAMIN A; CHOLECALCIFEROL; .ALPHA.-TOCOPHEROL

equate™ Anti-Itch Plus

Drug Facts

Active ingredient

Hydrocortisone 1%

Purpose

Anti-itch

Uses

- temporarily relieves itching associated with minor skin irritations, inflammation, and rashes due to:
  - eczema
  - psoriasis
  - poison ivy, oak, sumac
  - insect bites
  - detergents
  - jewelry
  - cosmetics
  - soaps
  - seborrheic dermatitis
- temporarily relieves external anal and genital itching
- other uses of this product should only be under the advice and supervision of a doctor

Warnings

For external use only

Do not use

- in the genital area if you have a vaginal discharge. Consult a doctor.
- for the treatment of diaper rash. Consult a doctor.

When using this product

- avoid contact with eyes
- do not use more than directed unless told to do so by a doctor
- do not put directly into the rectum by using fingers or any mechanical device or applicator

Stop use and ask a doctor if

- condition worsens, symptoms persist for more than 7 days or clear up and occur again within a few days, and do not begin use of any other hydrocortisone product unless you have asked a doctor
- rectal bleeding occurs

Keep out of reach of children.If swallowed, get medical help or contact a Poison Control Center right away.

Directions

- for itching of skin irritation, inflammation, and rashes:
  - adults and children 2 years of age and older: apply to affected area not more than 3 to 4 times daily
  - children under 2 years of age: ask a doctor
- for external anal and genital itching, adults :
  - when practical, clean the affected area with mild soap and warm water and rinse thoroughly
  - gently dry by patting or blotting with toilet tissue or a soft cloth before applying
  - apply to affected area not more than 3 to 4 times daily
  - children under 12 years of age: ask a doctor

Other information

- To open: unscrew cap, pull tab to remove foil seal, and screw cap back onto tube
- Store at 20° to 25°C (68° to 77°F)
- See carton or tube crimp for lot number and expiration date

Inactive ingredients

Aloe Barbadensis, Cetearyl Alcohol/Sodium Lauryl Sulfate/Sodium Cetearyl Sulfate, Chamomile (Anthemis Nobilis) Oil, Citric Acid, Corn (Zea Mays) Oil, Glycerin, Glyceryl Stearate, Isopropyl Palmitate, Maltodextrin, Methylparaben, Mineral Oil, Paraffin, Petrolatum, Propylene Glycol, Propylparaben, Purified Water, Stearyl Alcohol, Vitamin A (Retinyl Palmitate), Vitamin D (Cholecalciferol), Vitamin E (Tocopheryl Acetate).

Questions?

1-888-287-1915

DISTRIBUTED BY: Walmart Inc.,
Bentonville, AR 72716

PRINCIPAL DISPLAY PANEL - 28.4 g Tube Carton

NDC 49035-732-02

equate™

Compare
to Maximum
Strength
Cortizone•10®
Plus Active
Ingredient*

Anti-Itch
Plus
1% HYDROCORTISONE
ANTI-ITCH CREAM

MAXIMUM STRENGTH

With 12 healing
moisturizers including
aloe and vitamins A, D & E

Soothes and Relieves

- Dry, itchy skin
- Skin irritation and rashes
- Eczema and psoriasis

NET WT 1 OZ (28.4 g)